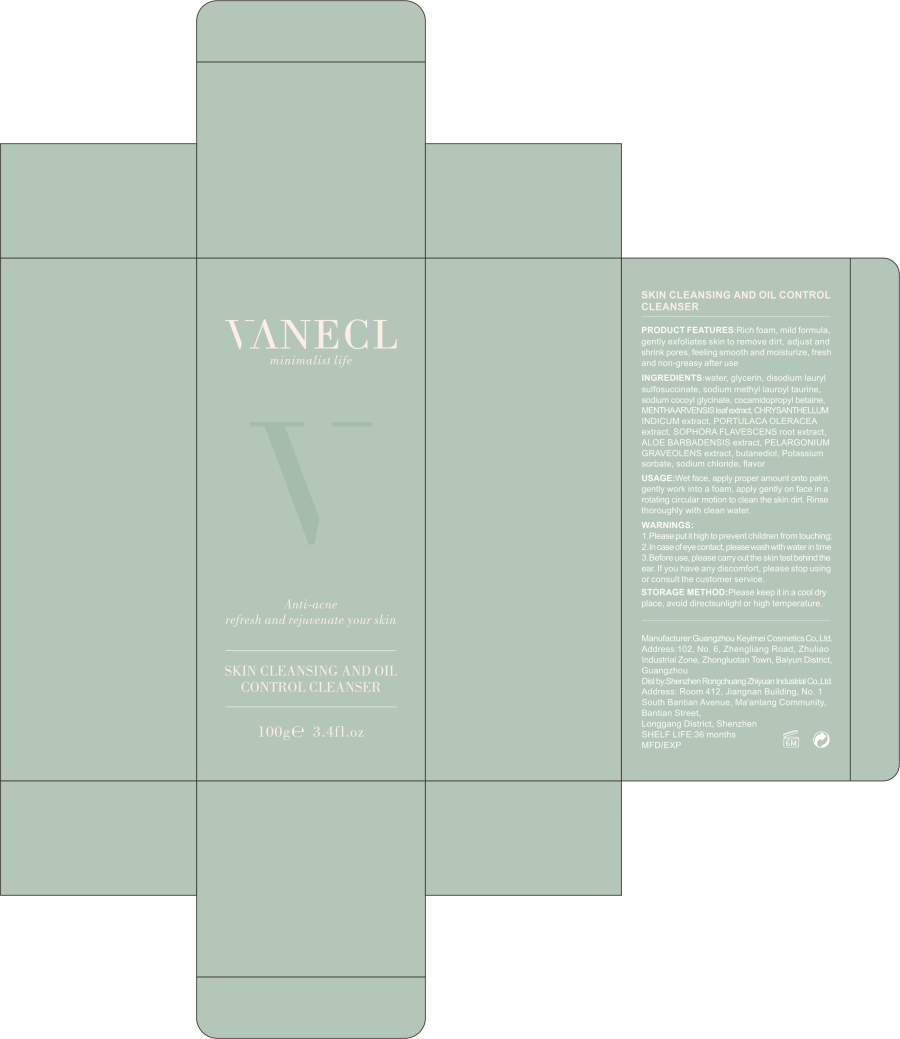 DRUG LABEL: Clear Skin Clarifying Cleanser
NDC: 80377-011 | Form: CREAM
Manufacturer: Shenzhen Rongchuang Zhiyuan Industrial Co., Ltd.
Category: otc | Type: HUMAN OTC DRUG LABEL
Date: 20200911

ACTIVE INGREDIENTS: MENTHOL 5 g/100 g; CHAMOMILE 6 g/100 g; ZINC OXIDE 2 g/100 g
INACTIVE INGREDIENTS: WATER; GLYCERIN

PACKAGE LABEL

100g a bottle DNC: 80377-011-01